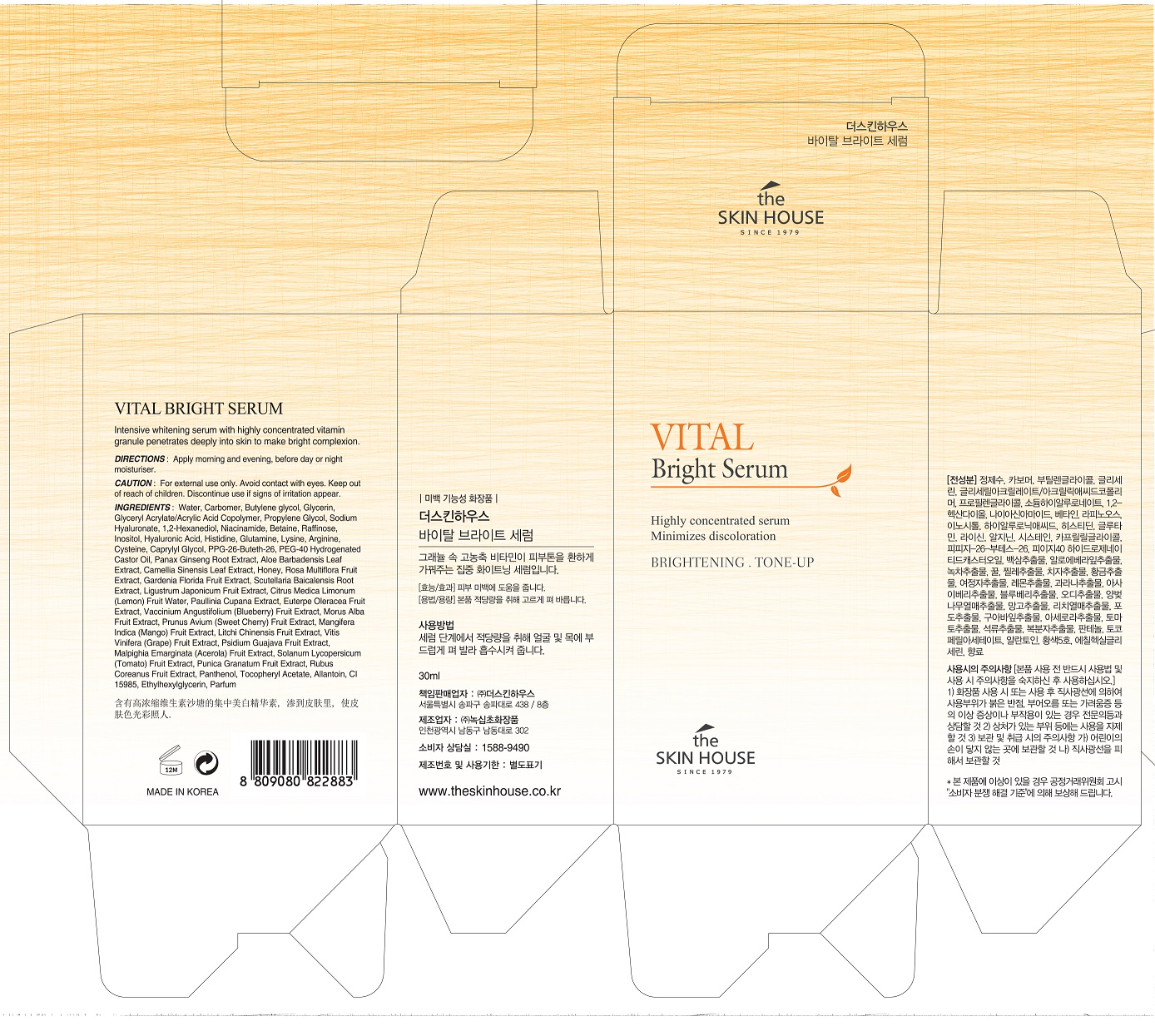 DRUG LABEL: THE SKIN HOUSE Vital BrightSerum
NDC: 73590-0028 | Form: LIQUID
Manufacturer: NOKSIBCHO cosmetic Co., Ltd.
Category: otc | Type: HUMAN OTC DRUG LABEL
Date: 20200330

ACTIVE INGREDIENTS: NIACINAMIDE 2 g/100 mL
INACTIVE INGREDIENTS: WATER

Drug Facts

ACTIVE INGREDIENT

Niacinamide

INACTIVE INGREDIENT

Water
Carbomer
Butylene glycol
Glyceryl Acrylate/Acrylic Acid Copolymer
Propylene Glycol
Glycerin
Sodium Hyaluronate
1,2-Hexanediol
Water
Betaine
Raffinose
Inositol
Hyaluronic Acid
Histidine
Glutamine
Lysine
Cysteine
Caprylyl Glycol
PPG-26-Buteth-26
PEG-40 Hydrogenated Castor Oil
Panax Ginseng Root Extract
Aloe Barbadensis Leaf Extract
Camellia Sinensis Leaf Extract
Honey
Rosa Multiflora Fruit Extract
Gardenia Florida Fruit Extract
Scutellaria Baicalensis Root Extract
Ligustrum Japonicum Fruit Extract
Citrus Medica Limonum (Lemon) Fruit Water
Paullinia Cupana Extract
Euterpe Oleracea Fruit Extract
Vaccinium Angustifolium (Blueberry) Fruit Extract
Morus Alba Fruit Extract
Prunus Avium (Sweet Cherry) Fruit Extract
Mangifera Indica (Mango) Fruit Extract
Litchi Chinensis Fruit Extract
Vitis Vinifera (Grape) Fruit Extract
Psidium Guajava Fruit Extract
Malpighia Emarginata (Acerola) Fruit Extract
Solanum Lycopersicum (Tomato) Fruit Extract
Punica Granatum Fruit Extract
Rubus Coreanus Fruit Extract
Panthenol
Tocopheryl Acetate
Arginine
Allantoin
CI 15985
Ethylhexylglycerin
Parfum

PURPOSE

skin brightening

keep out of reach of the children

INDICATIONS AND USAGE

apply proper amount to the skin

WARNINGS

For external use only
When using this product

■ if the following symptoms occurs after use, stop use and consult with a skin specialist

red specks, swelling, itching

■ don’t use on the part where there is injury, eczema, or dermatitis

Keep out of reach of children

■ if swallowed, get medical help or contact a person control center immediately